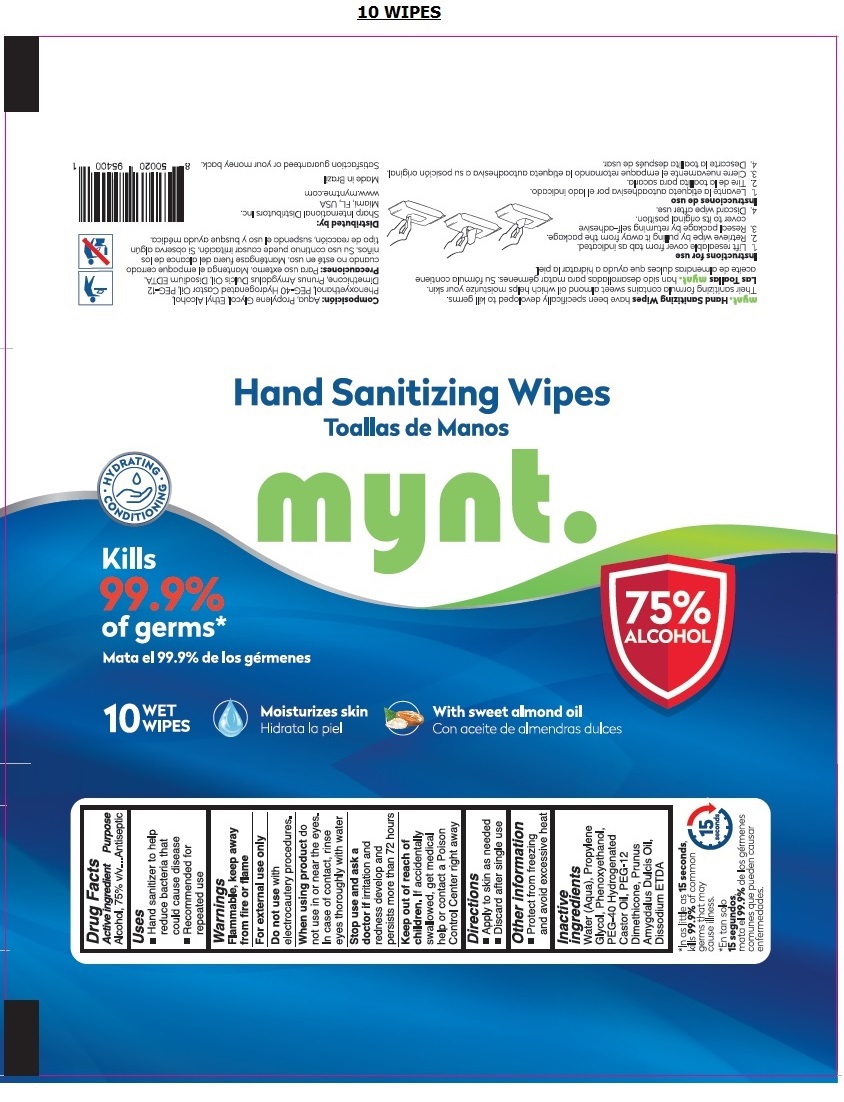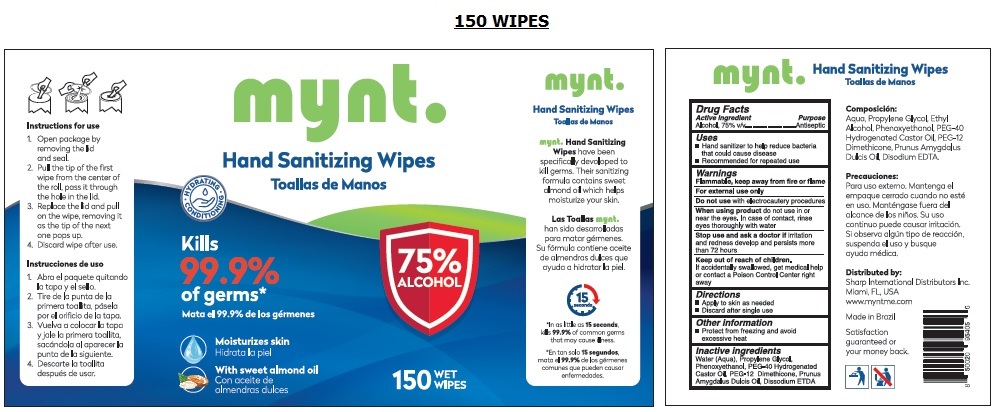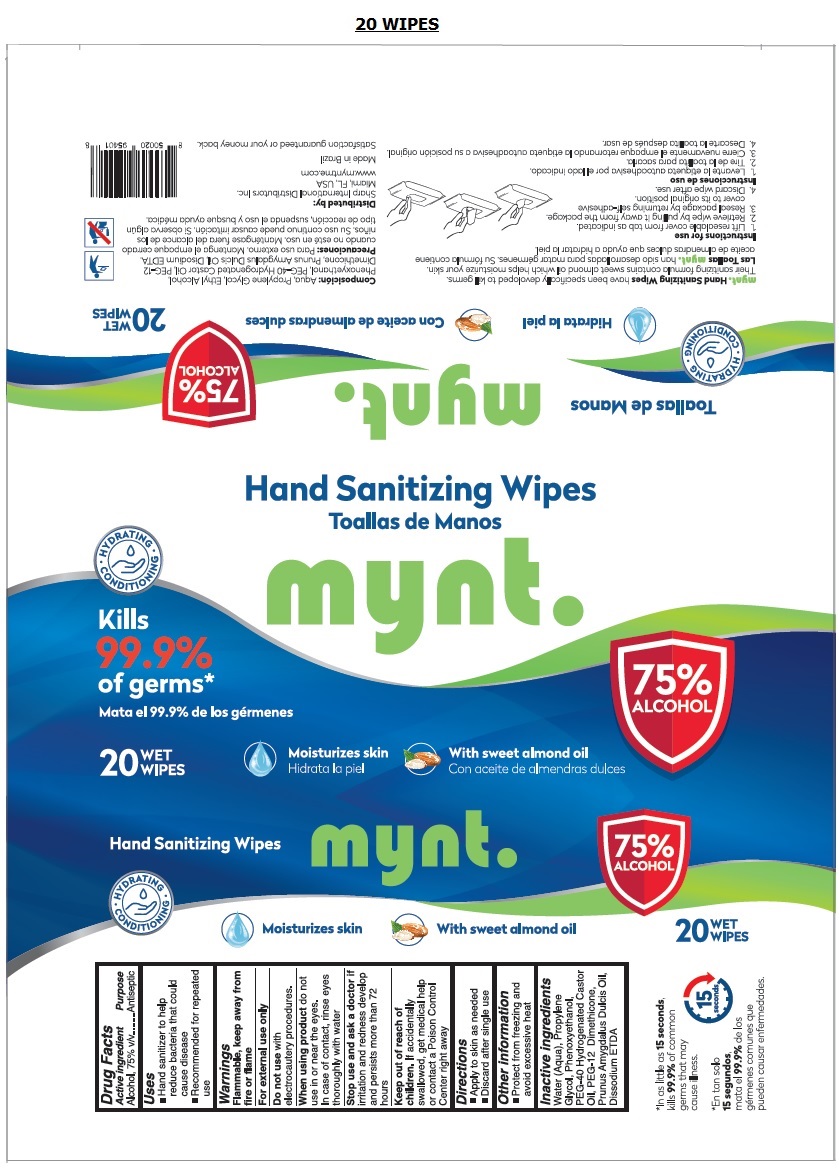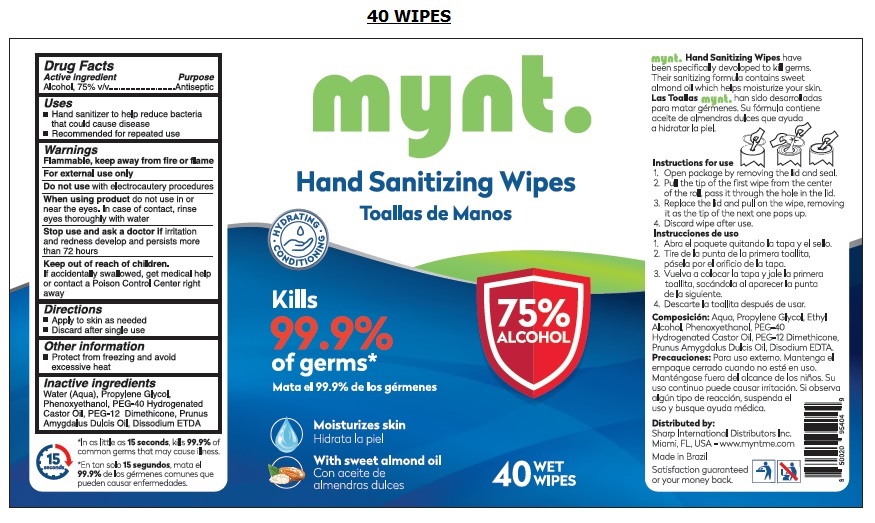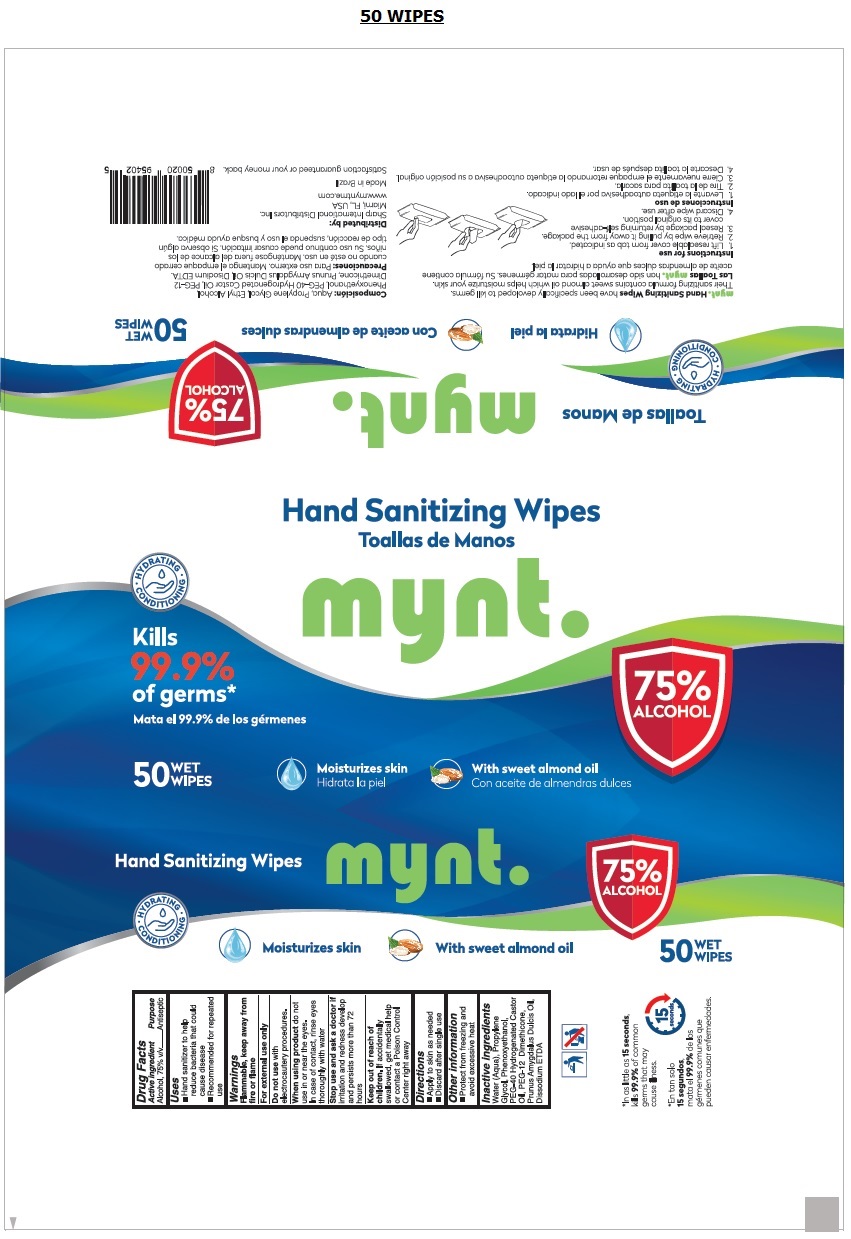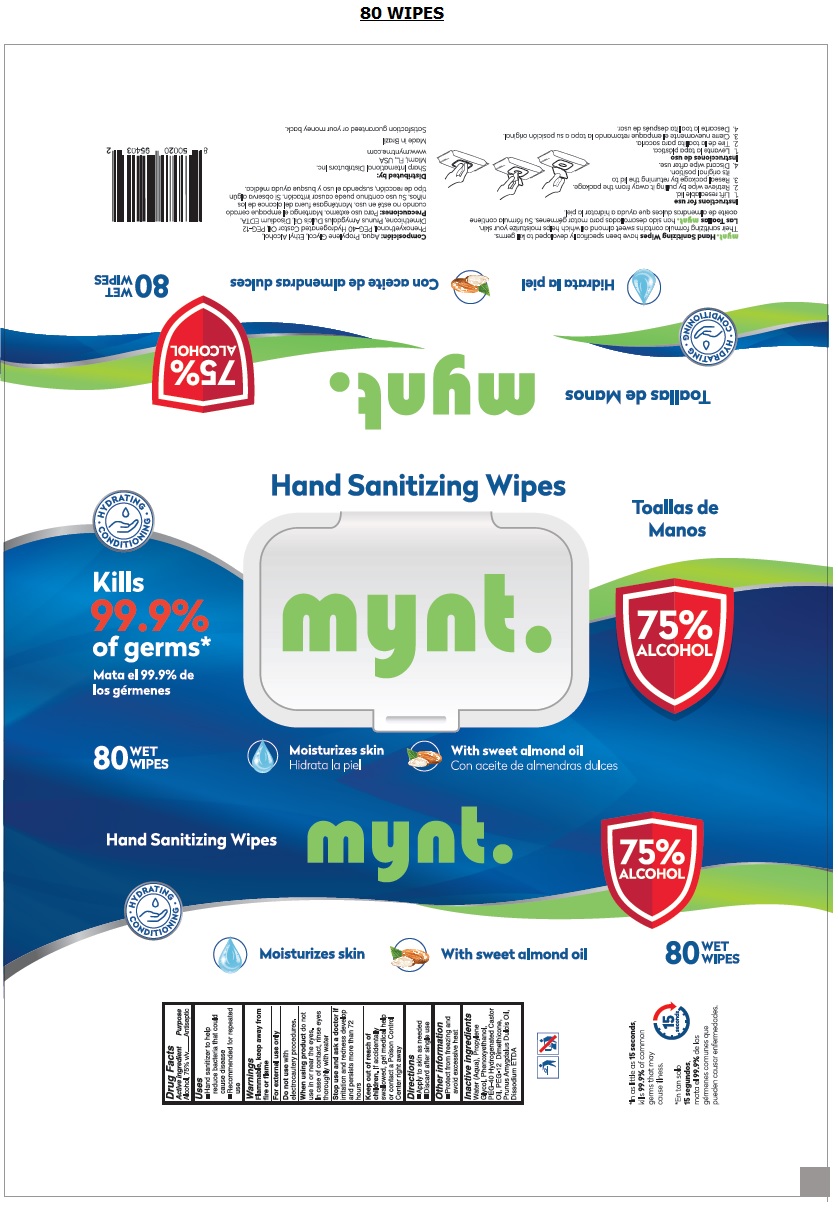 DRUG LABEL: Mynt. Hand Sanitizing Wipes
NDC: 79006-101 | Form: CLOTH
Manufacturer: Sharp International Distributors Inc.
Category: otc | Type: HUMAN OTC DRUG LABEL
Date: 20201020

ACTIVE INGREDIENTS: ALCOHOL 0.75 mL/1 mL
INACTIVE INGREDIENTS: WATER; PROPYLENE GLYCOL; PHENOXYETHANOL; POLYOXYL 40 HYDROGENATED CASTOR OIL; PEG-12 DIMETHICONE (300 CST); ALMOND OIL; EDETATE DISODIUM ANHYDROUS

mynt. Hand Sanitizing Wipes

Active ingredient

Alcohol, 75% v/v

Purpose

Antiseptic

Uses

• Hand sanitizer to help reduce bacteria that could cause disease

• Recommended for repeated use

Warnings

Flammable, keep away from fire or flame

For external use only

Do not use with electrocautery procedures.

When using product do not use in or near the eyes. In case of contact, rinse eyes thoroughly with water

Stop use and ask a doctor if irritation and redness develop and persists more than 72 hours

Keep out of reach of children.

If accidentally swallowed, get medical help or contact a Poison Control Center right away

Directions

• Apply to skin as needed

• Discard after single use

Other information

▪ Protect from freezing and avoid excessive heat

Inactive ingredients

Water (Aqua), Propylene Glycol, Phenoxyethanol, PEG-40 Hydrogenated Castor Oil, PEG-12 Dimethicone, Prunus Amygdalus Dulcis Oil, Dissodium ETDA

Kills 99.9% of germs*

Moisturizes skin

With sweet almond oil

mynt. Hand Sanitizing Wipes have been specifically developed to kill germs. Their sanitizing formula contains sweet almond oil which helps moisturize your skin.

*In as little as 15 seconds, kills 99.9% of common germs that may cause illness.

Instructions for use

1. Lift resealable cover from tab as indicated.

2. Retrieve wipe by pulling it away from the package.

3. Reseal package by returning self-adhesive cover to its original position.

4. Discard wipe after use.

Distributed by:

Sharp International Distributors Inc.

Miami - FL, USA - www.myntme.com

Made in Brazil

Satisfaction guaranteed or your money back.